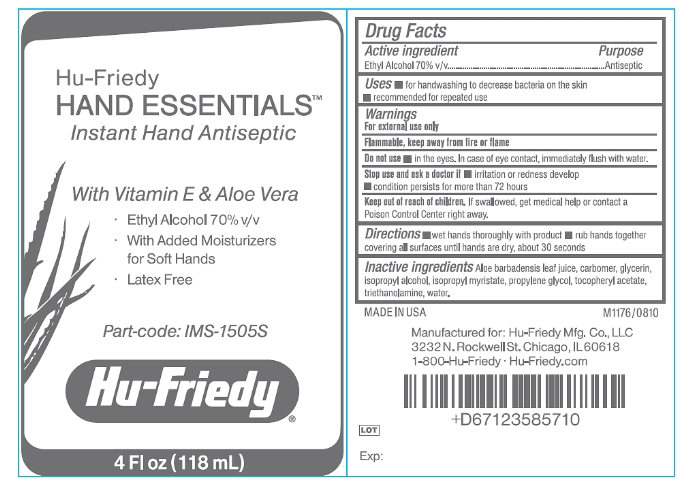 DRUG LABEL: Hand Essentials Instant Hand Antiseptic
NDC: 65626-206 | Form: GEL
Manufacturer: Hu-Friedy Mfg. Co., Inc.
Category: otc | Type: HUMAN OTC DRUG LABEL
Date: 20260112

ACTIVE INGREDIENTS: ALCOHOL 70 mL/100 mL
INACTIVE INGREDIENTS: ALOE VERA LEAF; CARBOMER 934; GLYCERIN; ISOPROPYL ALCOHOL; ISOPROPYL MYRISTATE; PROPYLENE GLYCOL; .ALPHA.-TOCOPHEROL ACETATE, D-; TROLAMINE; WATER

Hand Essentials Instant Hand Antiseptic

Active ingredient

Ethyl Alcohol 70% v/v

Purpose

Antiseptic

Uses

- for handwashing to decrease bacteria on skin.
- recommended for repeated use.

Warnings

For external use only.

Flammable, keep away from fire or flame.

Do not use

- in the eyes. In case of eye contact, immediately flush with water.

Stop use and ask a doctor if

- irritation or redness develop
- condition persists for more than 72 hours.

Keep out of reach of children.

If swallowed, get medical help or contact a Poison Control Center right away.

Directions

- wet hands thoroughly with product
- rub hands together covering all surfaces until hands are dry.

Inactive ingredients

Aloe barbadensis leaf juice, carbomer, glycerin, isopropyl alcohol, isopropyl myristate, propylene glycol, tocopheryl acetate, triethanolamine, water.

Package/Label Principal Display Panel

Hu-Friedy

HAND ESSENTIALS

Instant Hand Antiseptic

With Vitamin E & Aloe Vera

- Ethyl Alcohol 70% v/v
- With Added Moisturizers for soft hands
- Latex Free

Part-code: IMS-1505S

Hu-Friedy

4 Fl oz (118 mL)